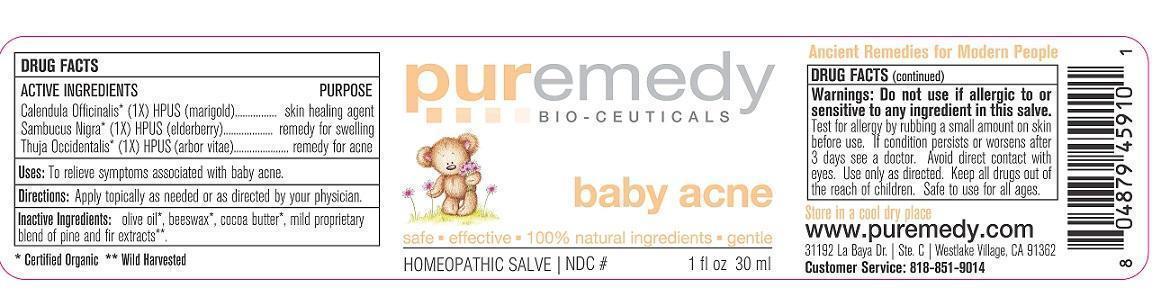 DRUG LABEL: BABY ACNE
NDC: 52810-214 | Form: SALVE
Manufacturer: PUREMEDY
Category: homeopathic | Type: HUMAN OTC DRUG LABEL
Date: 20240111

ACTIVE INGREDIENTS: CALENDULA OFFICINALIS FLOWER 1 [hp_X]/100 mL; SAMBUCUS NIGRA FLOWER 1 [hp_X]/100 mL; THUJA OCCIDENTALIS LEAF 1 [hp_X]/100 mL
INACTIVE INGREDIENTS: OLIVE OIL; YELLOW WAX; COCOA BUTTER; CANADA BALSAM

BABY ACNE (52810-214)

ACTIVE INGREDIENTS

ORG. CALENDULA OFFICINALIS (1X) HPUS) (MARIGOLD)

ORG. SAMBUCUS NIGRA (1X) HPUS (ELDER BARK AND FLOWER)

ORG. THUJA OCCIDENTALIS (1X) HPUS (ARBOR VITAE)

PURPOSE

SKIN HEALING AGENT

REMEDY FOR SWELLING

REMEDY FOR ACNE

INDICATIONS AND USAGE

USES: TO RELIEVE SYMPTOMS ASSOCIATED WITH BABY ACNE.

DOSAGE AND ADMINISTRATION

DIRECTIONS: APPLY TOPICALLY AS NEEDED OR AS DIRECTED BY YOUR PHYSICIAN.

INACTIVE INGREDIENT

INACTIVE INGREDIENTS: ORG. OLIVE OIL, ORG. BEESWAX, ORG. COCOA BUTTER, MILD PROPRIETARY BLEND OF PINE AND FIR EXTRACTS

WARNINGS

WARNINGS: DO NOT USE IF ALLERGIC TO OR SENSITIVE TO ANY INGREDIENT IN THIS SALVE. TEST FOR ALLERGY BY RUBBING A SMALL AMOUNT ON SKIN BEFORE USE. IF CONDITION PERSISTS OR WORSENS AFTER 3 DAYS SEE A DOCTOR. AVOID DIRECT CONTACT WITH EYES. USE ONLY AS DIRECTED. KEEP ALL DRUGS OUT OF USE OF CHILDREN. SAFE TO USE FOR ALL AGES.

KEEP ALL DRUGS OUT OF REACH OF CHILDREN.

STORAGE AND HANDLING

STORE IN A COOL DRY PLACE OR REFRIGERATE.

QUESTIONS

CUSTOMER SERVICE 818-851-9014